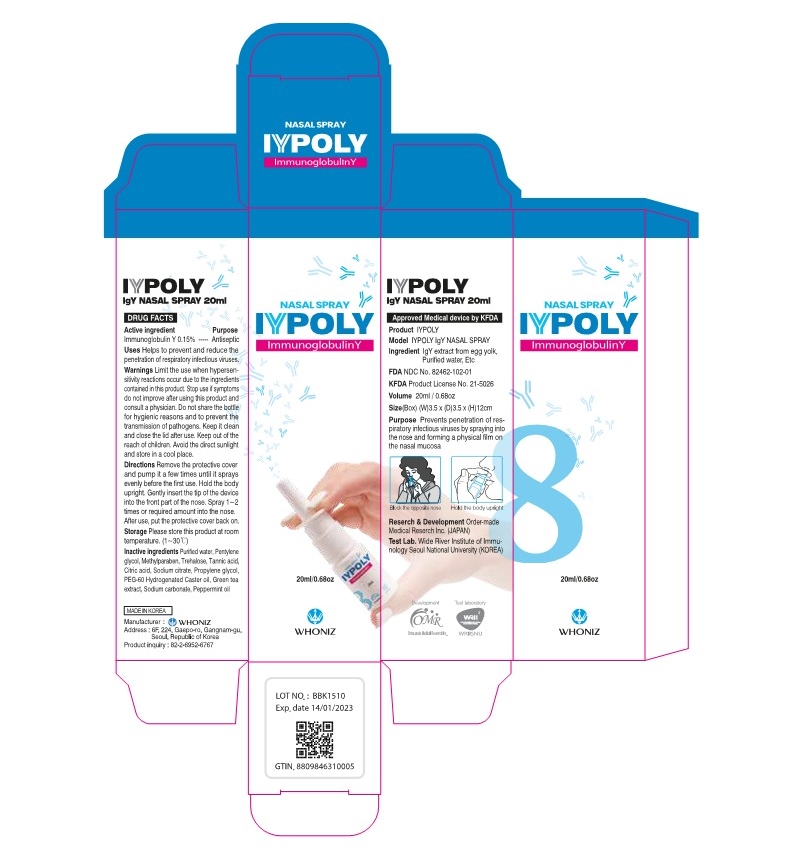 DRUG LABEL: IYPOLY
NDC: 82462-103 | Form: AEROSOL, SPRAY
Manufacturer: Whoniz
Category: otc | Type: HUMAN OTC DRUG LABEL
Date: 20220601

ACTIVE INGREDIENTS: PROPYLENE GLYCOL 1 g/100 mL; CITRIC ACID MONOHYDRATE 0.01 g/100 mL; HUMAN IMMUNOGLOBULIN G 0.15 g/100 mL
INACTIVE INGREDIENTS: TANNIC ACID; PEPPERMINT OIL TERPENELESS; WATER; GREEN TEA LEAF; METHYLPARABEN; PENTYLENE GLYCOL; POLYETHYLENE GLYCOL, UNSPECIFIED; TREHALOSE; SODIUM CARBONATE; TRISODIUM CITRATE DIHYDRATE

82462-103 IYPOLY

Purposes

Antiseptic

Active Ingredient

Immunoglobulin Y 0.15%

Citric Acid 0.01%

Propylene glycol 1%

Uses

Helps to prevent and reduce the penetration of respiratory infectious viruses.

Warnings

Limit the use when hypersensitivity reactions occur due to the ingredients contained in this product.

Warnings

Keep out of the reach of children

Warnings

Do not share the bottle for hygienic reasons and to prevent the transmission of pathogens

Warnings

Stop use if symptoms do not improve after using this product and consult a physician.

Warnings

Please store this product at room temperature. (1~30 ℃)

Directions

Remove the protective cover and pump it a few times until it sprays evenly before the first use. Hold the body upright. Gently insert the tip of the device into the front part of the nose. Spray 1~2 times or required amount into the nose. After use, put the protective cover back on.

Inactive Ingredients

Purified water , Pentyleneglycol , Methylparaben, Trehalose, Tannicacid , Citricacid,

Sodiumcitrate, Propyleneglyco, PEG60 Hydrogenated, Casteroil , Greentea extract ,

Sodiumcarbonate , Peppermint oil